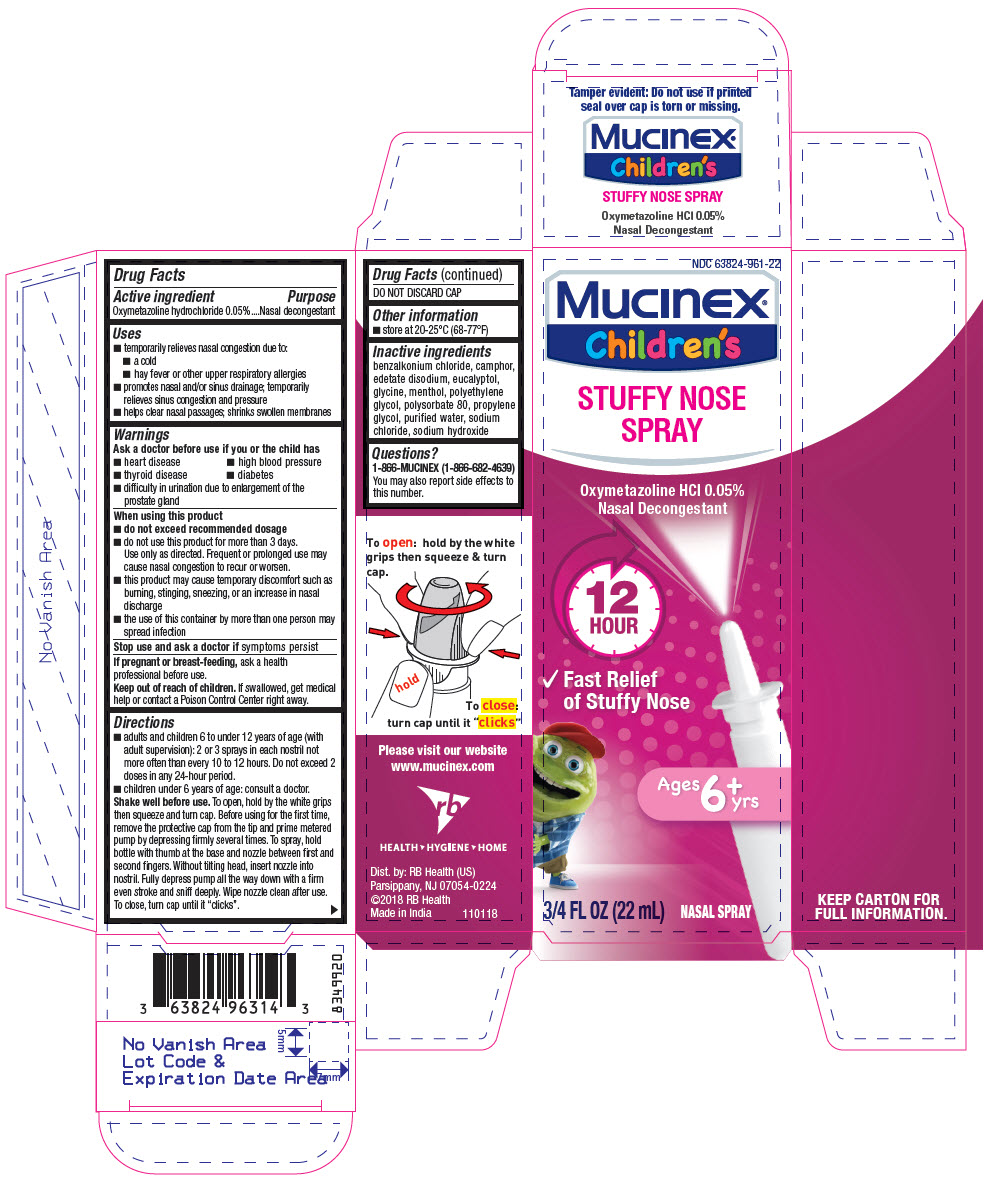 DRUG LABEL: MUCINEX Childrens Stuffy Nose
NDC: 63824-961 | Form: SOLUTION
Manufacturer: RB Health (US) LLC
Category: otc | Type: HUMAN OTC DRUG LABEL
Date: 20241227

ACTIVE INGREDIENTS: OXYMETAZOLINE HYDROCHLORIDE 0.05 g/100 mL
INACTIVE INGREDIENTS: BENZALKONIUM CHLORIDE; EDETATE DISODIUM; EUCALYPTOL; GLYCINE; MENTHOL, UNSPECIFIED FORM; POLYETHYLENE GLYCOL, UNSPECIFIED; POLYSORBATE 80; PROPYLENE GLYCOL; WATER; SODIUM CHLORIDE; SODIUM HYDROXIDE; CAMPHOR (SYNTHETIC)

MUCINEX® Children's Stuffy Nose Spray

Drug Facts

Active ingredient

Oxymetazoline hydrochloride 0.05%

Purpose

Nasal decongestant

Uses

- temporarily relieves nasal congestion due to:
  - a cold
  - hay fever or other upper respiratory allergies
- promotes nasal and sinus drainage; temporarily relieves sinus congestion and pressure
- helps clear nasal passages; shrinks swollen membranes

Warnings

Ask a doctor before use if you or the child has

- heart disease
- high blood pressure
- thyroid disease
- diabetes
- difficulty in urination due to enlargement of the prostate gland

When using this product

- do not exceed recommended dosage
- do not use this product for more than 3 days.
  Use only as directed. Frequent or prolonged use may cause nasal congestion to recur or worsen
- this product may cause temporary discomfort such as burning, stinging, sneezing, or an increase in nasal discharge
- the use of this container by more than one person may spread infection

Stop use and ask a doctor ifsymptoms persist

PREGNANCY OR BREAST FEEDING

If pregnant or breast-feeding,ask a health professional before use.

Keep out of reach of children.If swallowed, get medical help or contact a Poison Control Center right away.

Directions

- adults and children 6 to under 12 years of age (with adult supervision): 2 or 3 sprays in each nostril, not more often than every 10 to 12 hours. Do not exceed 2 doses in any 24-hour period.
- children under 6 years of age: consult a doctor.

Shake well before use.To open, hold by the white grips then squeeze and turn cap. Before using for the first time, remove the protective cap from the tip and prime metered pump by depressing firmly several times. To spray, hold bottle with thumb at the base and nozzle between first and second fingers. Without tilting head, insert nozzle into nostril. Fully depress pump all the way down with a firm even stroke and sniff deeply. Wipe nozzle clean after use. To close, turn cap until it "clicks".

DO NOT DISCARD CAP

Other information

- store between 20-25°C (68-77°F)

Inactive ingredients

benzalkonium chloride, camphor, edetate disodium, eucalyptol, glycine, menthol, polyethylene glycol, polysorbate 80, propylene glycol, purified water, sodium chloride, sodium hydroxide

Questions?

1-866-MUCINEX (1-866-682-4639)
You may also report side effects to this number.

Dist. by: RB Health (US)
Parsippany, NJ 07054-0224

Made in India

PRINCIPAL DISPLAY PANEL - 22 mL Bottle Carton

NDC 63824-961-22

Mucinex®

Children's

STUFFY NOSE
SPRAY

Oxymetazoline HCl 0.05%
Nasal Decongestant

12
HOUR

- Fast Relief
  of Stuffy Nose

Ages 6+
yrs

3/4 FL OZ (22 mL)
NASAL SPRAY